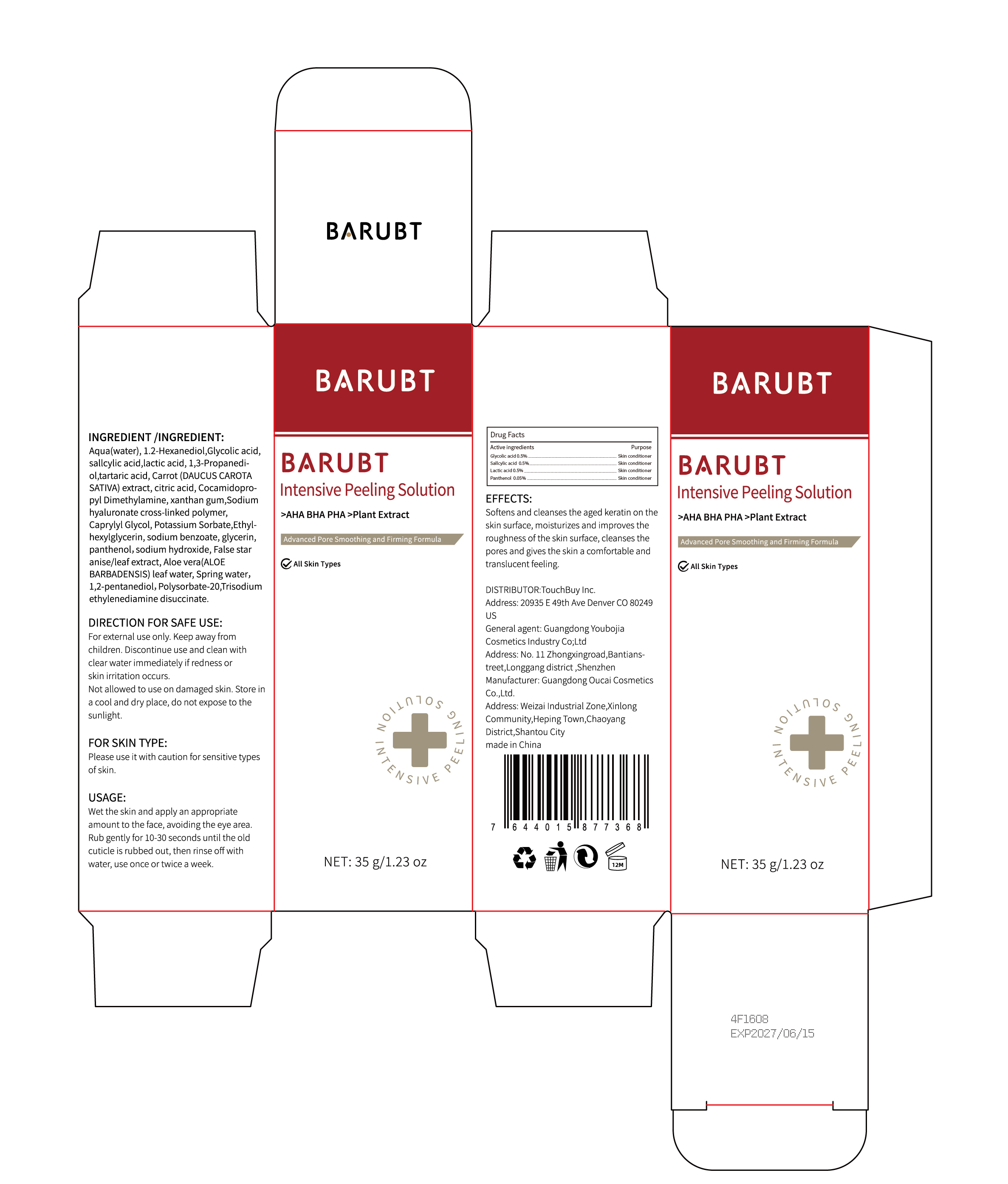 DRUG LABEL: BARUBT Intensive Peeling Solution
NDC: 84712-011 | Form: LOTION
Manufacturer: Guangdong Youbaijia Cosmetic Industry Co., Ltd
Category: otc | Type: HUMAN OTC DRUG LABEL
Date: 20240913

ACTIVE INGREDIENTS: PANTHENOL 0.0175 g/35 mL; LACTIC ACID 0.175 g/35 mL; GLYCOLIC ACID 0.175 g/35 mL
INACTIVE INGREDIENTS: XANTHAN GUM 0.035 g/35 mL; TARTARIC ACID 0.07 g/35 mL

ACTIVE INGREDIENT

Glycolic acid 0.5%
sallcylic acid 0.5%
lactic acid 0.5%
panthenol 0.05%

DO NOT USE

on damaged or broken skin

Keep away from children. Do not swallow.

PURPOSE

Softens and cleanses the aged keratin on the skin surface

QUESTIONS

Contact name: Jessie Peng
Company phone number: +1 818 579 7288
Company e-mail: jessie@registeragentllc.com

STOP USE

Discontinue use and clean with clear water immediately if redness or skin irritation occurs.

WHEN USING

keep out of eyes. Rinse with water to remove.

INACTIVE INGREDIENT

Aqua(water)
1.2-Hexanediol
1,3-Propanedi-ol
tartaric acid
Carrot (DAUCUS CAROTASATIVA) extract
citric acid
Cocamidopro-pyl Dimethylamine
xanthan gum
Sodiumhyaluronate cross-linked polymer
Caprylyl Glycol
Potassium Sorbate
Ethyl-hexylglycerin
sodium benzoate
glycerin
sodium hydroxide
False staranise/leaf extract
Aloe vera(ALOEBARBADENSIS) leaf water
Spring water
1,2-pentanediol
Polysorbate-20
Trisodiumethylenediamine disuccinate

DOSAGE AND ADMINISTRATION

Wet the skin and apply an appropriate amount to the face, avoiding the eye area.Rub gently for 10-30 seconds until the old cuticle is rubbed out, then rinse off with water, use once or twice a week.

STORAGE AND HANDLING

Keep away from light and in adry place.

WARNINGS

For external use only.

INDICATIONS AND USAGE

Softens and cleanses the aged keratin on the skin surface, moisturizes and improves the roughness of the skin surface, cleanses the pores and gives the skin a comfortable and translucent feeling